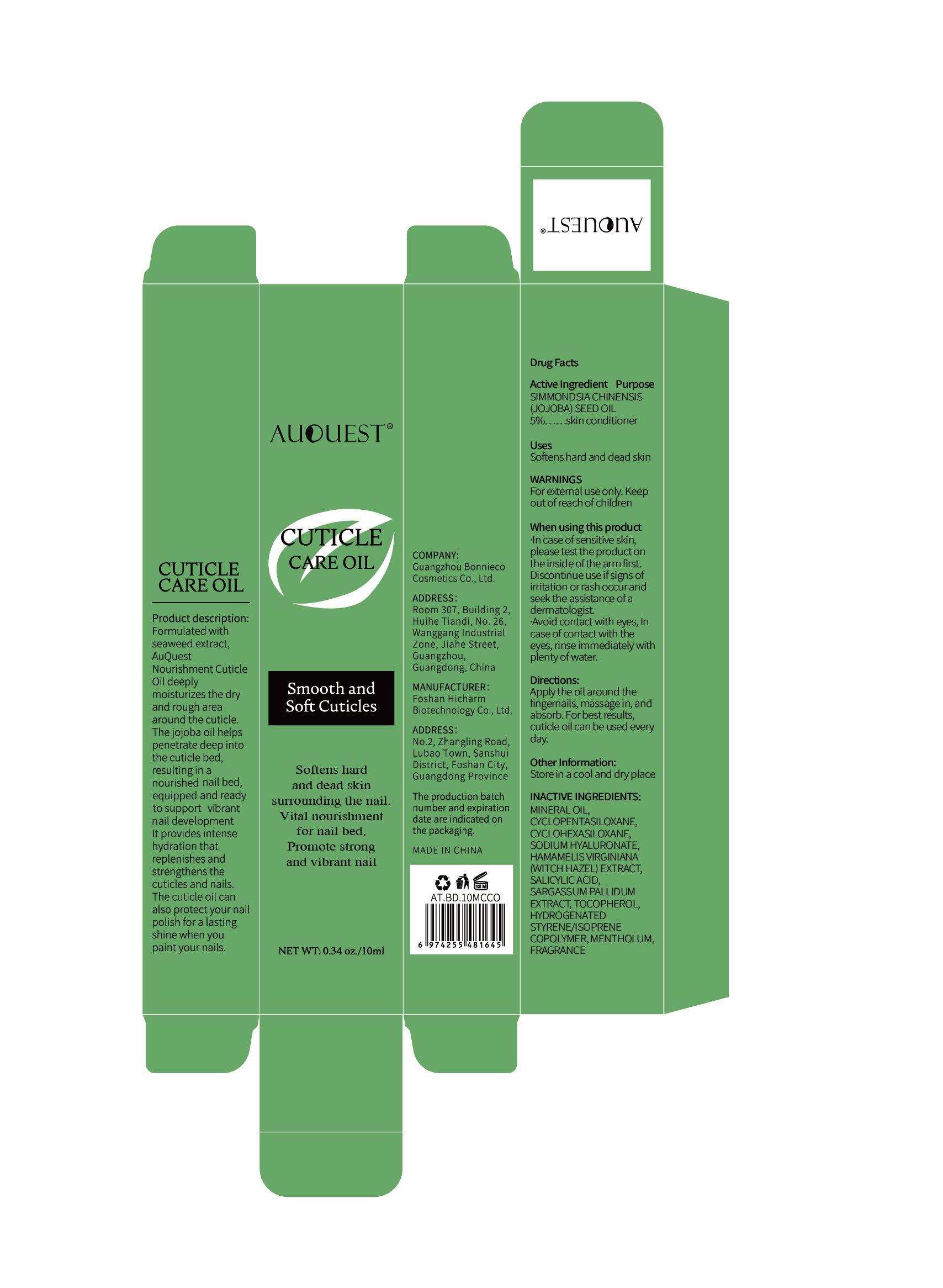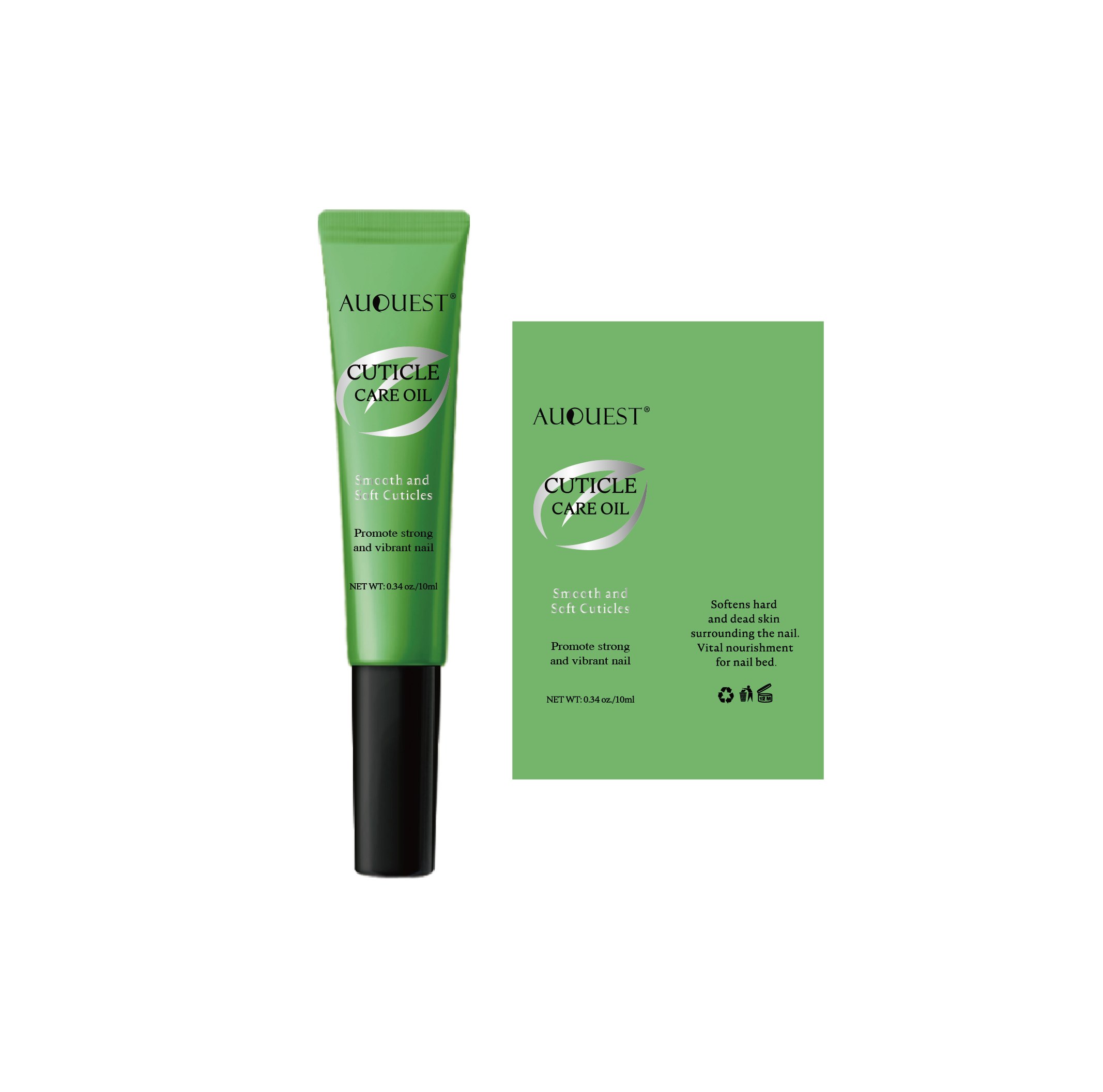 DRUG LABEL: AuQuest Smooth and Soft Cuticles
NDC: 84186-012 | Form: OIL
Manufacturer: Guangzhou Bonnieco Cosmetics Co., Ltd
Category: otc | Type: HUMAN OTC DRUG LABEL
Date: 20240402

ACTIVE INGREDIENTS: CYCLOMETHICONE 5 5 g/100 mL
INACTIVE INGREDIENTS: JOJOBA OIL; TOCOPHEROL; HYALURONATE SODIUM; SARGASSUM PALLIDUM; MINERAL OIL; CYCLOMETHICONE 6; HAMAMELIS VIRGINIANA TOP; MENTHOL; SALICYLIC ACID; ISOPRENE; FRAGRANCE 13576

84186-012

Active Ingredient

CYCLOPENTASILOXANE 5%

Purpose

Skin conditioner, Nail Restoration

Use

Softens hard and dead skin

Warnings

For external use only. Keepoutof reach of children

Do not use

ln case of sensitive skin,please test the productonthe inside of the arm first.Discontinue use if signs ofirritation orrash occurandseek the assistance ofadermatologist.-ln case of sensitive skin,please test the productonthe inside of the arm first.Discontinue use if signs ofirritation orrash occurandseek the assistance ofadermatologist.eyes, rinse immediately withplenty of water.

When Using

In case of contact with the eyes, rinse immediately with plenty of water.

Stop Use

If discomfort arises, please immediately stop using the product and seek the assistance of a dermatologist.

Ask Doctor

If discomfort arises, please immediately stop using the product and seek the assistance of a dermatologist.

Keep Oot Of Reach Of Children

Keep out of reach of children. If swallowed call emergency services.

Directions

Apply the oil aroundthe fingernails,massage in, andabsorb.For bestresults, cuticle oilcan be used every day.

Other information

Store in a cool and dry place

Inactive ingredients

MINERAL OIL, CYCLOHEXASILOXANE, SIMMONDSIA CHINENSIS (JOJOBA) SEED OIL, SODIUM HYALURONATE, HAMAMELIS VIRGINIANA (WITCH HAZEL) EXTRACT, SALICYLIC ACID, SARGASSUM PALLIDUM EXTRACT, TOCOPHEROL, HYDROGENATED STYRENE/ISOPRENE COPOLYMER, MENTHOLUM, FRAGRANCE